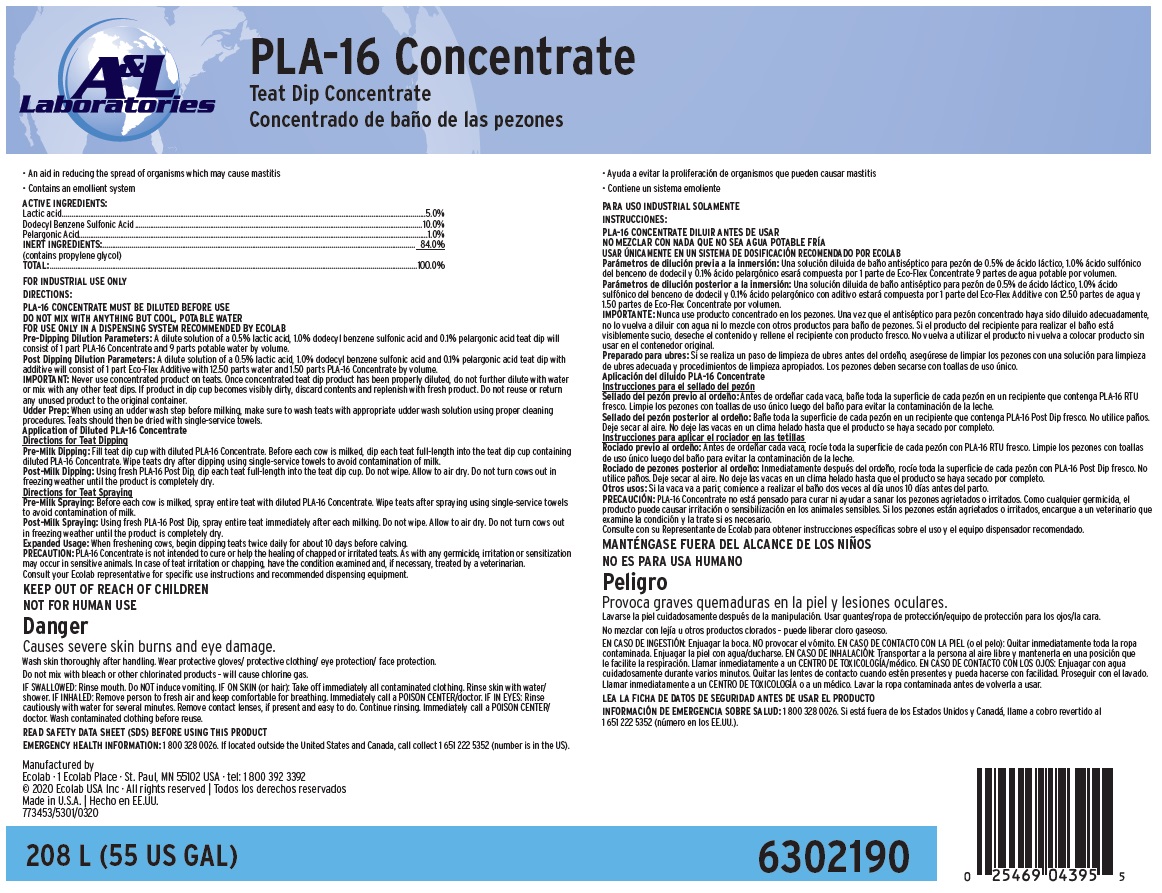 DRUG LABEL: PLA-16 CONC
NDC: 47593-590 | Form: SOLUTION
Manufacturer: Ecolab Inc.
Category: animal | Type: OTC ANIMAL DRUG LABEL
Date: 20251116

ACTIVE INGREDIENTS: LACTIC ACID 50 mg/1 mL; DODECYLBENZENESULFONIC ACID 100 mg/1 mL; PELARGONIC ACID 10 mg/1 mL
INACTIVE INGREDIENTS: WATER; PROPYLENE GLYCOL

SAFE HANDLING WARNING

Danger

Causes severe skin burns and eye damage.

Wash skin thoroughly after handling. Wear protective gloves/ protective clothing/ eye protection/ face protection.

Do not mix with bleach or other chlorinated products – will cause chlorine gas.

IF SWALLOWED: Rinse mouth. Do NOT induce vomiting. IF ON SKIN (or hair): Take off immediately all contaminated clothing. Rinse skin with water/shower. IF INHALED: Remove person to fresh air and keep comfortable for breathing. Immediately call a POISON CENTER/doctor. IF IN EYES: Rinse cautiously with water for several minutes. Remove contact lenses, if present and easy to do. Continue rinsing. Immediately call a POISON CENTER/doctor. Wash contaminated clothing before reuse.

DIRECTIONS:

PLA-16 CONCENTRATE MUST BE DILUTED BEFORE USE

DO NOT MIX WITH ANYTHING BUT COOL, POTABLE WATER

FOR USE ONLY IN A DISPENSING SYSTEM RECOMMENDED BY ECOLAB

Pre-Dipping Dilution Parameters: A dilute solution of a 0.5% lactic acid, 1.0% dodecyl benzene sulfonic acid and 0.1% pelargonic acid teat dip will consist of 1 part PLA-16 Concentrate and 9 parts potable water by volume.

Post Dipping Dilution Parameters: A dilute solution of a 0.5% lactic acid, 1.0% dodecyl benzene sulfonic acid and 0.1% pelargonic acid teat dip with additive will consist of 1 part Eco-Flex Additive with 12.50 parts water and 1.50 parts PLA-16 Concentrate by volume.

IMPORTANT: Never use concentrated product on teats. Once concentrated teat dip product has been properly diluted, do not further dilute with water or mix with any other teat dips. If product in dip cup becomes visibly dirty, discard contents and replenish with fresh product. Do not reuse or return any unused product to the original container.

Udder Prep: When using an udder wash step before milking, make sure to wash teats with appropriate udder wash solution using proper cleaning procedures. Teats should then be dried with single-service towels.

Application of Diluted PLA-16 Concentrate

Directions for Teat Dipping

Pre-Milk Dipping: Fill teat dip cup with diluted PLA-16 Concentrate. Before each cow is milked, dip each teat full-length into the teat dip cup containing diluted PLA-16 Concentrate. Wipe teats dry after dipping using single-service towels to avoid contamination of milk.

Post-Milk Dipping: Using fresh PLA-16 Post Dip, dip each teat full-length into the teat dip cup. Do not wipe. Allow to air dry. Do not turn cows out in freezing weather until the product is completely dry.

Directions for Teat Spraying

Pre-Milk Spraying: Before each cow is milked, spray entire teat with diluted PLA-16 Concentrate. Wipe teats after spraying using single-service towels to avoid contamination of milk.

Post-Milk Spraying: Using fresh PLA-16 Post Dip, spray entire teat immediately after each milking. Do not wipe. Allow to air dry. Do not turn cows out in freezing weather until the product is completely dry.

Expanded Usage: When freshening cows, begin dipping teats twice daily for about 10 days before calving.

PRECAUTION: PLA-16 Concentrate is not intended to cure or help the healing of chapped or irritated teats. As with any germicide, irritation or sensitization may occur in sensitive animals. In case of teat irritation or chapping, have the condition examined and, if necessary, treated by a veterinarian.

Consult your Ecolab representative for specific use instructions and recommended dispensing equipment.

OTHER SAFETY INFORMATION

FOR INDUSTRIAL USE ONLY

KEEP OUT OF REACH OF CHILDREN

NOT FOR HUMAN USE

READ SAFETY DATA SHEET (SDS) BEFORE USING THIS PRODUCT

EMERGENCY HEALTH INFORMATION: 1 800 328 0026. If located outside the United States and Canada, call collect 1 651 222 5352 (number is in the US).

Principal display panel and representative label

PLA-16 Concentrate

Teat Dip Concentrate

• Contains an emollient system

• An aid in reducing the spread of organisms which may cause mastitis

ACTIVE INGREDIENTS:

Lactic acid........................................................... ..... .......... ..... 5.0%

Dodecyl Benzene Sulfonic Acid........................................... .... 10.0%

Pelargonic Acid............................................................... ........ 1.0%

INERT INGREDIENTS.................................................................. 84.0%

(contains propylene glycol)

TOTAL....................................................... ..... ..... ................ 100.0%

Manufactured by

Ecolab · 1 Ecolab Place · St. Paul, MN 55102 USA · tel: 1 800 392 3392

© 2020 Ecolab USA Inc · All rights reserved | Todos los derechos reservados

Made in U.S.A. | Hecho en EE.UU.

773453/5301/0320

208 L (55 US GAL)